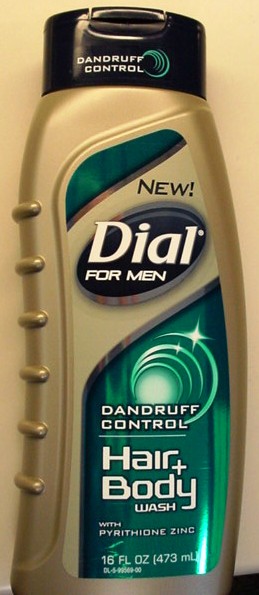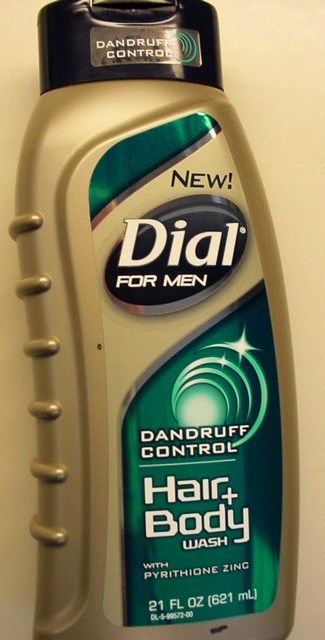 DRUG LABEL: Dial For Men Dandruff Control Hair and Body Wash
NDC: 54340-003 | Form: SOLUTION
Manufacturer: The Dial Corporation
Category: otc | Type: HUMAN OTC DRUG LABEL
Date: 20110124

ACTIVE INGREDIENTS: Pyrithione Zinc 0.95 g/100 g
INACTIVE INGREDIENTS: Water; Sodium Laureth Sulfate; Cocamidopropyl Betaine; Carbomer 1342; Glycerin; Laureth-7; Carboxymethylcellulose Sodium; Sodium Hydroxide; DMDM Hydantoin; Sodium Chloride

Drug Facts

Active Ingredient - Pyrithione Zinc 0.95%

Purpose - Anti dandruff
Advanced Pyrithione Zinc formula provides a head-to-toe clean.
Helps prevent flakes and relieves scalp itch,dryness, and irritation.

INDICATIONS AND USAGE

Use Helps prevent recurrence of flaking and itching associated with dandruff

Warnings For external use only

When using this product avoid contact with eyes. If contact occurs,rinse eyes thoroughly with water.

Stop use and ask a doctor if condition worsens or does not improve after regular use of this product as directed.

Keep out of reach of children if swallowed get medical help or contact a poison control center right away.

Directions

- For best results use at least twice a week or as directed by a doctor.
- Wet hair and body, massage on to scalp and affected areas in place of your regular soap or body wash,rinse,and repeat if desired.

INACTIVE INGREDIENT

Inactive ingredients WATER SODIUM LAURETH SULFATE,COCAMIDOPROPYL BETAINE,ACRYLATES COPOLYMER,GLYCERIN, FRAGRANCE,PEG-7 GLYCERYL COCOATE, POLYQUATERNIUM-7,SODIUM POLYNAPHTHALENESULFONATE,CELLULOSE GUM,SODIUM HYDROXIDE,DMDM HYDANTOIN,SODIUM CHLORIDE,CITRIC ACID,BLUE 1,YELLOW5.

Questions? 1-800-258-DIAL(3425)

PACKAGE LABEL

dialformen-16 oz

dialformen-21 oz